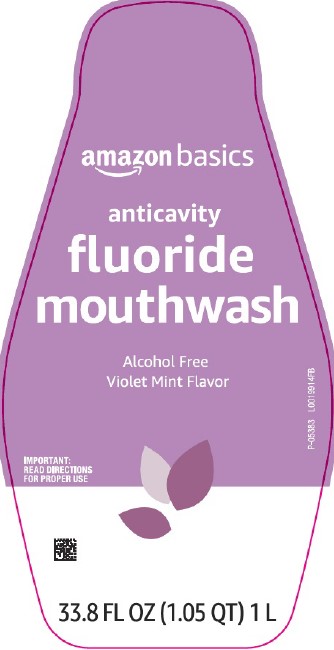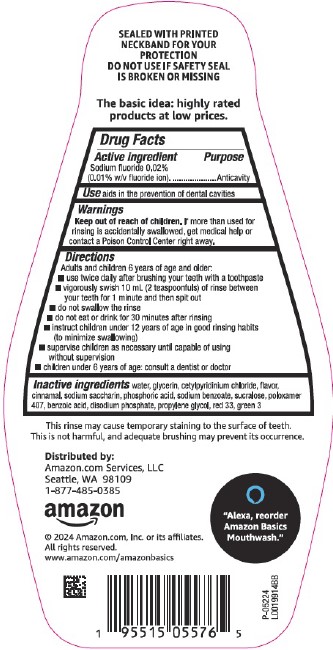 DRUG LABEL: Alcohol-Free Anticavity
NDC: 72288-482 | Form: LIQUID
Manufacturer: Amazon.Com Services LLC
Category: otc | Type: HUMAN OTC DRUG LABEL
Date: 20250519

ACTIVE INGREDIENTS: SODIUM FLUORIDE 0.1 mg/1 mL
INACTIVE INGREDIENTS: WATER; GLYCERIN; CETYLPYRIDINIUM CHLORIDE; CINNAMALDEHYDE; SACCHARIN SODIUM; PHOSPHORIC ACID; SODIUM BENZOATE; SUCRALOSE; POLOXAMER 407; BENZOIC ACID; SODIUM PHOSPHATE, DIBASIC, ANHYDROUS; PROPYLENE GLYCOL; D&C RED NO. 33; FD&C GREEN NO. 3

Basics 482.002/482AC
Alcohol Free Fluoride Violet Mint Mouthwash

Claims

SEALED WITH PRINTED NECKBAND FOR YOUR PROTECTION

DO NOT USE IF SAFETY SEAL IS BROKEN OR MISSING

The basic idea: highly rated products at low prices.

Active ingredient

Sodium fluoride 0.02% (0.01% w/v fluoride ion)

Purpose

Anticavity

Use

aids in the prevention of dental cavities

Warnings

for this product

Keep out of reach of children.

If more than used for rinsing is accidentally swallowed, get medical help or contact a Poison Control Center right away.

Directions

Adults and children 6 years of age and older:

- use twice daily after brushing your teeth with a toothpaste
- vigorously swish 10 mL (2 teaspoonfuls) of rinse between your teeth for 1 minute and then spit out
- do not swallow the rinse
- do not eat or drink for 30 minutes after rinsing
- instruct children under 12 years of age in good rinsing habits (to minimize swallowing)
- supervise children as necessary until capable of using without supervision
- children under 6 years of age: consult a dentist or doctor

Inactive ingredients

water, glycerin, cetylpyridinium chloride, flavor, cinnamal, sodium saccharin, phosphoric acid, sodium benzoate, sucralose, poloxamer 407, benzoic acid, disodium phosphate, propylene glycol, red 33, green 3

Disclaimer

This rinse may cause temporary staining to the surface of teeth.

This is not harmful, and adequate brushing may prevent its occurrence.

Adverse Reactions

DISTRIBUTED BY:

Amazon.com, Services, Inc

Seattle, WA 98109

1-877-485-0385

amazon

© 2024 Amazon.com, Inc. or its affiliates.

All rights reserved.

www.amazon.com/amazonbasics

"Alexa, reorder Amazon Basics Mouthwash."

principal display panel

amazon basics

anticavity

fluoride mouthwash

Alcohol Free

Violet Mint Flavor

IMPORTANT: RED DIRECTIONS FOR PROPER USE

33.8 FL OZ (1.05 QT) 1 L